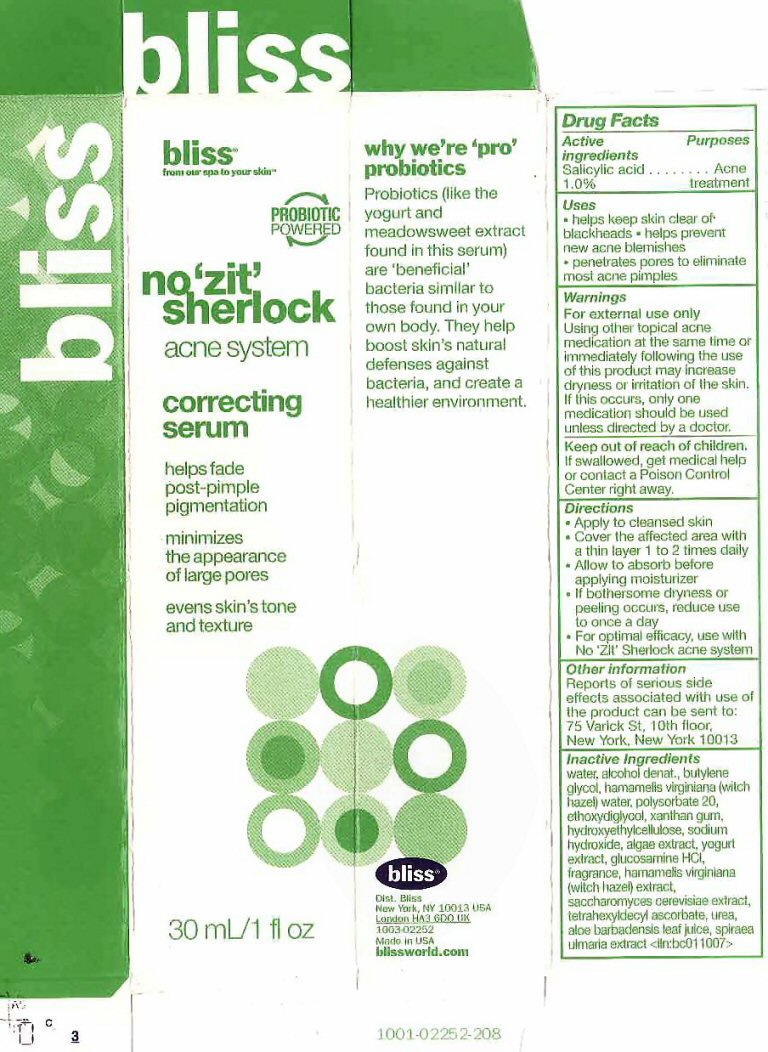 DRUG LABEL: no zit sherlock acne
NDC: 67038-106 | Form: GEL
Manufacturer: Bliss World LLC
Category: otc | Type: HUMAN OTC DRUG LABEL
Date: 20120604

ACTIVE INGREDIENTS: SALICYLIC ACID 1 mL/100 mL
INACTIVE INGREDIENTS: WATER; ALCOHOL; BUTYLENE GLYCOL; HAMAMELIS VIRGINIANA TOP WATER; POLYSORBATE 20; DIETHYLENE GLYCOL MONOETHYL ETHER; XANTHAN GUM; SODIUM HYDROXIDE; GLUCOSAMINE HYDROCHLORIDE; HAMAMELIS VIRGINIANA TOP; SACCHAROMYCES CEREVISIAE; TETRAHEXYLDECYL ASCORBATE; UREA; ALOE VERA LEAF; FILIPENDULA ULMARIA WHOLE

Active Ingredients

Drug Facts

Active Ingredients

Salicylic acid 1.0%

Purposes

Acne treatment

Keep out of reach of children. If swallowed, get medical help or contact a Poison Control Center right away.

Uses

- helps keep skin clear of blackheads
- helps prevent new acne blemishes
- penetrates pores to eliminate most acne pimples

Warnings

For external use only
Using other topical acne medication at the same time or immediately following the use of this product may increase dryness or irritation of the skin. If this occurs, only one medication should be used unless directed by a doctor.

Directions

- Apply to cleansed skin
- Cover the affected area with a thin layer 1 to 2 times a day
- Allow to absorb before applying moisturizer
- If bothersome dryness or peeling occurs, reduce use to once daily
- For optimal efficacy, use with No 'Zit' Sherlock acne system

Other information

Reports on serious side effects associated with the use of the product can be sent to: 75 Varick St. 10th Floor, New York, New York 10013

Inactive Ingredients

water, alcohol denat., butylene glycol, hamamelis virginiana (witch hazel) water, polysorbate 20, ethoxydiglycol, xanthan gum, hydroxyethylcellulose, sodium hydroxide, algae extract, yogurt extract, glucosamine HCL, fragrance, hamamelis virginiana (witch hazel) extract, saccharomyces cerevisiae extract, tetrahexyldecyl ascorbate, urea, aloe barbadensis leaf juice, spiraea ulmaria extract

Package Label

bliss from our spa to your skin PROBIOTIC POWERED
no 'zit' sherlock acne system correcting serum

helps fade post-pimple pigmentation minimizes the appearance of large pores evens skin's tone and texture

why we're 'pro' probiotics Probiotics (like the yogurt and meadowsweet extract found in this moisturizer) are 'beneficial' bacteria similar to those found in your own body. They help boost skin's natural defenses against bacteria and create a healthier environment.
bliss dist Bliss New York NY 10013 USA London HA3 6DO UK 1003-02250 Made in USA blissworld.com
30mL/1 fl oz 1001-02252-208